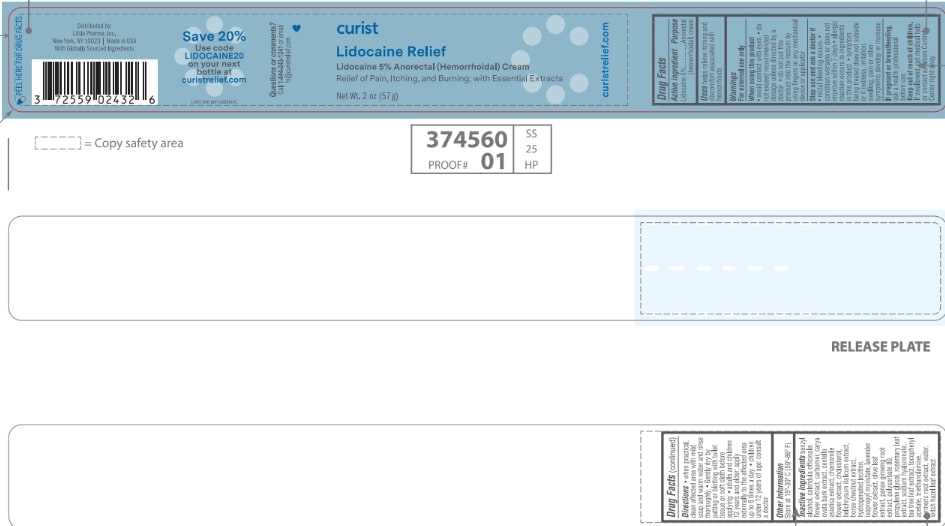 DRUG LABEL: Curist Lidocaine Relief
NDC: 72559-024 | Form: CREAM
Manufacturer: Little Pharma, Inc.
Category: otc | Type: HUMAN OTC DRUG LABEL
Date: 20241120

ACTIVE INGREDIENTS: LIDOCAINE 5 g/100 g
INACTIVE INGREDIENTS: HYDROGENATED SOYBEAN LECITHIN; CHOLESTEROL; CARBOMER 940; ROSEMARY; ALPHA-TOCOPHEROL ACETATE; TROLAMINE; HELICHRYSUM ITALICUM FLOWER; ISOPROPYL MYRISTATE; LAVANDULA ANGUSTIFOLIA FLOWER; TURMERIC; WATER; HAMAMELIS VIRGINIANA LEAF; POLYSORBATE 80; PROPYLENE GLYCOL; HYALURONATE SODIUM; MELALEUCA ALTERNIFOLIA LEAF; BENZYL ALCOHOL; CALENDULA OFFICINALIS FLOWER; CARYA OVATA BARK; CENTELLA ASIATICA TRITERPENOIDS; CHAMOMILE; HORSE CHESTNUT; OLEA EUROPAEA LEAF; ASIAN GINSENG

Curist Lidocaine Relief (with Essential Extracts)

Drug Facts

Active ingredient

Lidocaine 5%

Purpose

Anorectal (hemorrhoidal) cream

Uses
helps relieve itching and discomfort associated with hemorrhoids

Warnings
For external use only

When using this product

- avoid contact with eyes
- do not exceed recommended dosage unless directed by a doctor
- do not put this product into the rectum by using fingers or any mechanical device or applicator

Stop use and ask a doctor if

- rectal bleeding occurs
- condition worsens or does not improve within 7 days
- allergic reaction occurs to ingredients in this product
- symptom being treated does not subside or if redness, irritation, swelling, pain or other symptoms develop or increase

PREGNANCY OR BREAST FEEDING

If pregnant or breastfeeding, ask a health professional before use.

Keep out of reach of children. If swallowed, get medical help or contact a Poison Control Center right away

Directions

- when practical, clean affected area with mild soap and warm water and rinse thoroughly
- Gently dry by patting or blotting with toilet tissue or soft cloth before applying
- adults and children 12 years and older: apply externally to the affected area up to 6 times a day
- children under 12 years of age: consult a doctor

Other information

Store at 15°-30° C (59°-86° F)

INACTIVE INGREDIENT

Inactive ingredients benzyl alcohol, calendula officinalis flower extract, carbomer, carya ovata bark extract, centella asiatica extract, chamomile flower extract, cholesterol, helichrysum italicum extract, horse chestnut extract, hydrogenated lecithin, isopropyl myristate, lavender flower extract, olive leaf extract, panax ginseng root extract, polysorbate 80, propylene glycol, rosemary leaf extract, sodium hyaluronate, tea tree leaf extract, tocopheryl acetate, triethanolamine, turmeric root extract, water, witch hazel leaf extract

curistrelief.com

PEEL HERE FOR DRUG FACTS

Distributed by:
Little Pharma, Inc.
New York, NY 10023 | Made in USA

With Globally Sourced Ingredients

Save 20%

Use code

LIDOCAINE20

on your next bottle at

curistrelief.com

Limit one per customer.

Questions or comments?

Call 1-844-243-1241 or email hi@curistrelief.com

PACKAGE LABEL

curist
Lidocaine Relief
Lidocaine 5% Anorectal (Hemorrhoidal) Cream
Relief of Pain, Itching and Burning; with Essential Extracts

Net Wt. 2 oz (57 g)